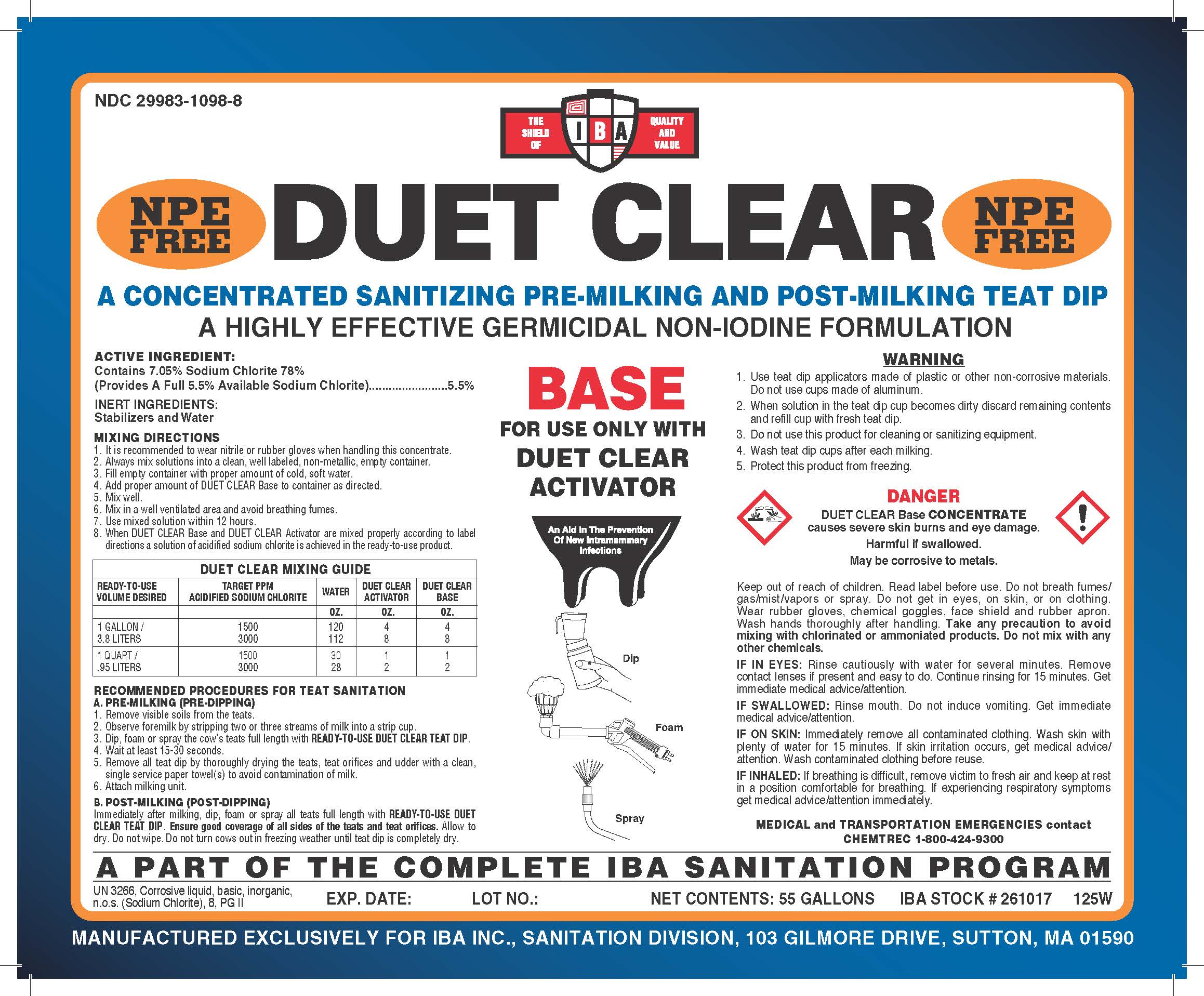 DRUG LABEL: Duet Clear Base
NDC: 29983-1098 | Form: LIQUID
Manufacturer: IBA
Category: animal | Type: OTC ANIMAL DRUG LABEL
Date: 20260213

ACTIVE INGREDIENTS: SODIUM CHLORITE 5.5 kg/100 kg

Duet Clear Base

Active Ingredient

Sodium Chlorite 5.5%

Inert Ingredients

Stabilizers & Water

Mixing Directions

1. It is recommended to wear nitrile or rubber gloves when handling a concentrate to avoid staining hands.

2. Always mix solutions into a clean, well labeled, non-metalic, empty container.

3. Fill empty container with proper amount of cold, soft water.

4. Add proper amount of Duet Base to container as directed.

5. Add proper amount of Duet Activator to container as directed.

6. Mix in a well ventilated area and avoid breathing fumes.

7. Use mixed solution within 12 hours.

8. When Duet Base and Duet Activator are mixed properly, according to the label directions, a solution of acidified sodium chlorite is achieved in the ready-to-use product.

Recommended Procedures for Teat Dip Sanitation

A. Pre-Milking (Pre-Dipping)

1. Remove visible soils from the teats.

2. Observe foremilk by stripping two or three streams of milk into a strip cup.

3. Dip or spray the cow's teats full length with Ready-to-Use Duet Teat Dip.

4. Wait at least 15-30 seconds.

5. Remove all teat dip by thoroughly drying the teats, test orifices & udder with a clean, single service paper towel(s) to avoid contamination of milk.

6. Attach milking unit.

B. Post-Milking (Post-Dipping)

Immediately after milking, dip or spray all teats full length with Ready-to-Use Duet Teat Dip. Ensure good coverage of all sides of the teats and teat orifices. Allow to dry. Do not wipe. Do not turn cows out in freezing weather until teat dip is completely dry.

Warning

1. Use teat dip applicators made of plastic or other non-corrosive materials. Do not use cups made of aluminum.

2. When solution in the teat dip cup becomes dirty, discard remaining contents and refill cup with fresh teat dip.

3. Do not use this product for cleaning or sanitizing equipment.

4. Wash teat dip cups after each milking.

5. Protect this product from freezing.

Danger

Causes severe skin burns & eye damage.

Harmful if swallowed.

May be corrosive to metals.

First Aid

If in Eyes: Rinse cautiously with water for several minutes. Remove contact lenses if present & easy to do. Continue rinsing for 15 minutes. Get immediate medical advice/attention.

If Swallowed: Rinse mouth. Do not induce vomitting. Get immediate medical advice/attention.

If on Skin: Immediately remove all contaminated clothing. Wash with plenty of water for 15 minutes. If skin irritation occurs, get medical advice/attention. Wash contaminated clothing before use.

If Inhaled: If breathing is difficult, remove victim to fresh air & keep at rest in a position comfortable for breathing. If experiencing respiratory symptoms get medical advice/attention immediatley.

Caution

Keep out of reach of children.

Duet Clear Base

A concentrated sanitizing pre-milking & post-milking teat dip.